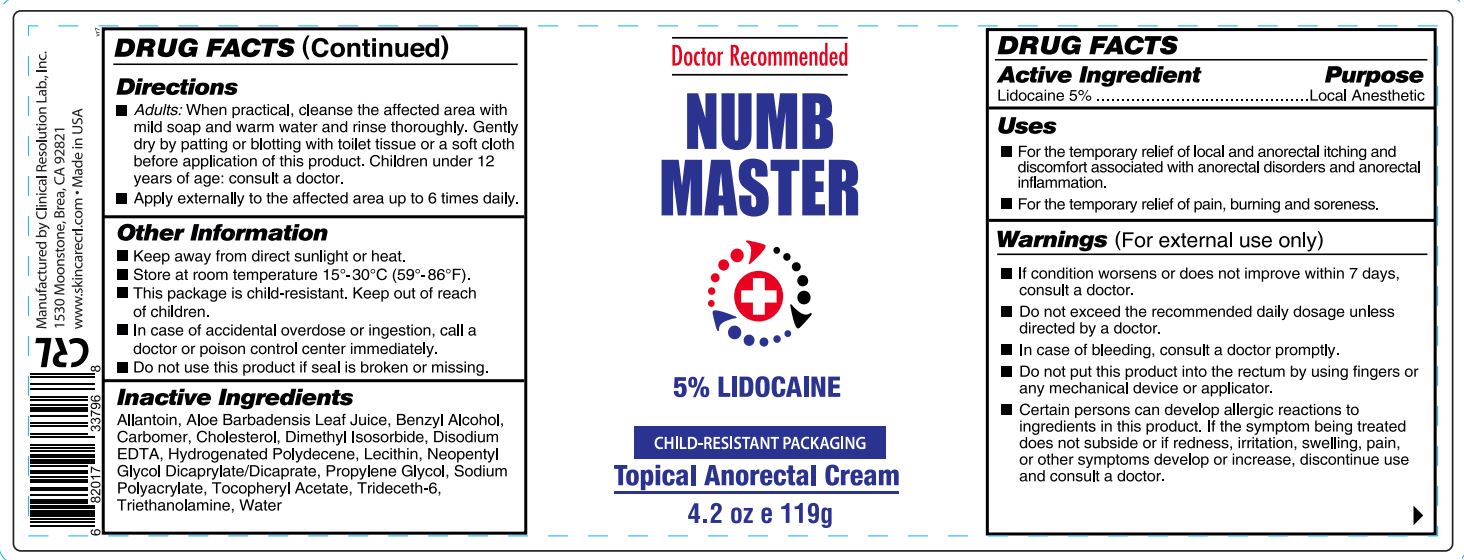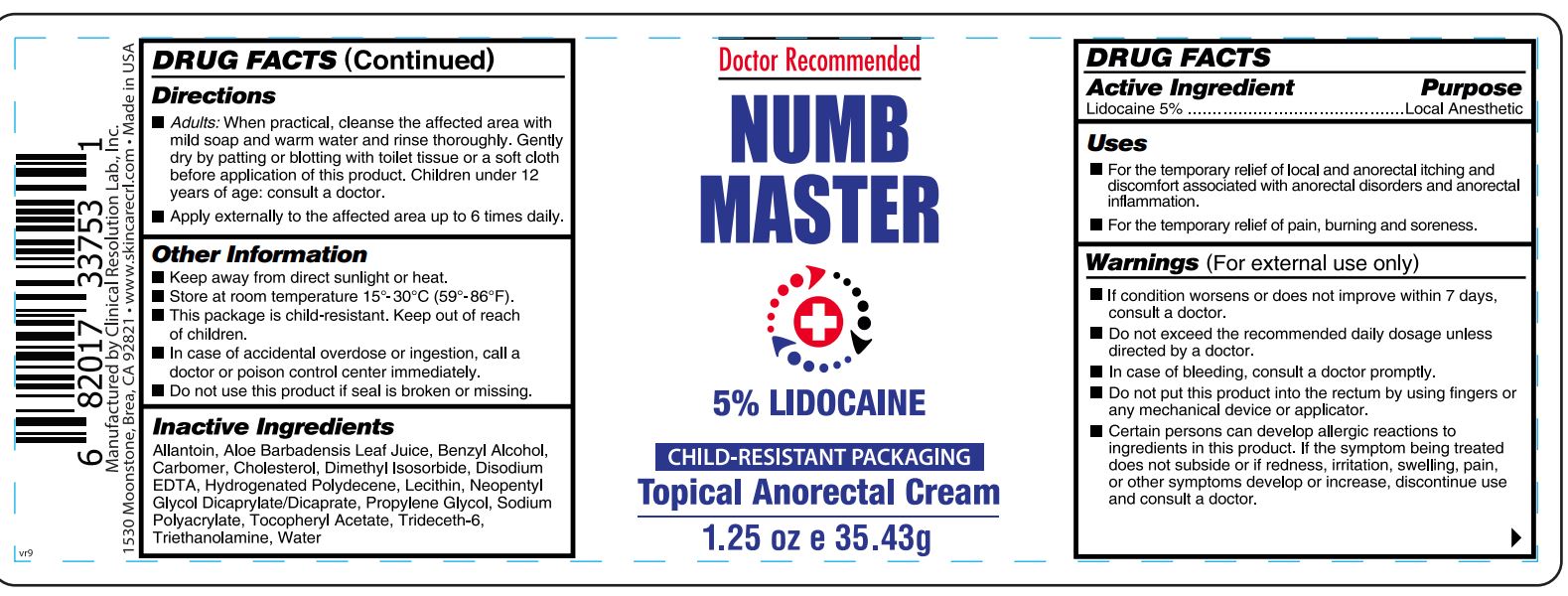 DRUG LABEL: Numb Master
NDC: 63742-032 | Form: CREAM
Manufacturer: Clinical Resolution Laboratory, Inc.
Category: otc | Type: HUMAN OTC DRUG LABEL
Date: 20260209

ACTIVE INGREDIENTS: LIDOCAINE 50 mg/1 g
INACTIVE INGREDIENTS: ALLANTOIN; ALOE VERA LEAF; BENZYL ALCOHOL; CARBOMER HOMOPOLYMER, UNSPECIFIED TYPE; CHOLESTEROL; DIMETHYL ISOSORBIDE; EDETATE DISODIUM ANHYDROUS; NEOPENTYL GLYCOL DICAPRYLATE/DICAPRATE; PROPYLENE GLYCOL; WATER; .ALPHA.-TOCOPHEROL ACETATE; TRIDECETH-6; TROLAMINE

Numb Master

Active Ingredient

Lidocaine 5%

Purpose

Local Anesthetic

Uses:

for the temporary relief of local and anorectal discomfort associated with anorectal disorders or inflammation.

Warnings

(For external use only)

Do not use

this product if

- pregnant or breastfeeding, ask a health professional before use.
- in case of accidental overdose, get medical help or contact the Poison Control Center immediately.
- tamper evident "Do not use this product" if seal is broken or missing.

When using this product

- do not exceed the recommended daily dosage unless directed by a doctor.
- certain persons can develop allergic reactions to ingredients in this product.
- do not put this product into the rectum by using finger or any medical device or applicator.

Stop use and ask a doctor if

the symptom being treated does not subside, or if redness, irritation, swelling, pain, or other symptoms develop or increase.

Keep out of reach of children

In case of accidental ingestion, seek medical attention immediately.

Directions

- Adults:When practical, cleanse the affected area with mild soap and warm water and rinse thoroughly. Gently dry by patting or blotting with toilet tissue or a soft cloth, before application of this product.
- Apply up to 6 times a day.
- Children under 12 years of age: consult a doctor.

Other Information

- keep away from direct sunlight or heat.
- store in room temperature (59-86°F/15-30°C)

Inactive Ingredients

Allantoin, Aloe Barbadensis Leaf Juice, Benzyl Alcohol, Carbomer, Cholesterol, Dimethyl Isosorbide, Disodium EDTA, Hydrogenated Polydecene, Lecithin, Neopentyl Glycol Dicaprylate/Dicaprate, Propylene Glycol, Water, Sodium Polyacrylate, Tocopheryl Acetate, Trideceth-6, Triethanolamine